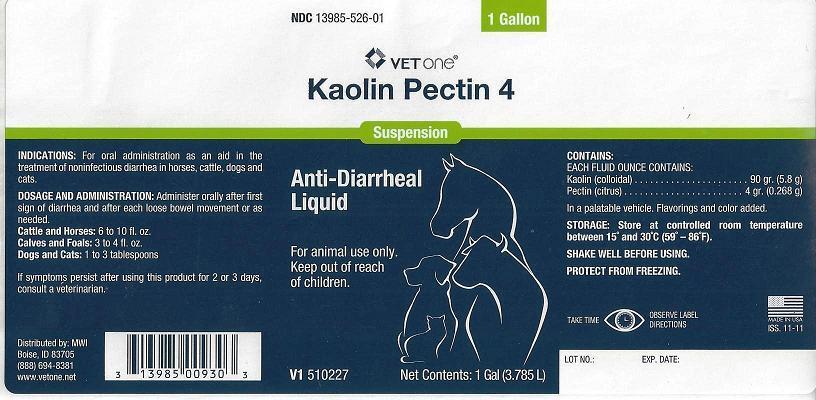 DRUG LABEL: Kaolin Pectin 4
NDC: 13985-526 | Form: SUSPENSION
Manufacturer: MWI/VetOne
Category: animal | Type: OTC ANIMAL DRUG LABEL
Date: 20130916

ACTIVE INGREDIENTS: KAOLIN 196 mg/1 mL; PECTIN, CITRUS 9 mg/1 mL
INACTIVE INGREDIENTS: GUAR GUM; METHYLPARABEN; POTASSIUM SORBATE; SACCHARIN SODIUM; PROPYLPARABEN; FD&C RED NO. 40; WATER

VETONE® Kaolin Pectin 4 Anti-Diarrheal Liquid

NDC 13985-526-01 1 Gallon VET ONE Kaolin Pectin 4 Suspension Anti-Diarrheal Liquid

For animal use only.

Keep out of reach of children.

V1 510227

Net Contents: 1 Gal (3.785L)

INDICATIONS:

For oral administration as an aid in the treatment of noninfectious diarrhea in horses, cattle, dogs and cats.

DOSAGE AND ADMINISTRATION:

Administer orally after first sign of diarrhea and after each loose bowel movement or as needed.

Cattle and Horses: 6 to 10 fl. oz.

Calves and Foals: 3 to 4 fl. oz.

Dogs and Cats: 1 to 3 tablespoons

If symptoms persist after using this product for 2 or 3 days, consult a veterinarian.

Distributed by: MWI

Boise, ID 83705

(888) 694-8381

www.vetone.net

CONTAINS:

EACH FLUID OUNCE CONTAINS:

Kaolin (colloidal) ... 90 gr. (5.8 g)

Pectin (citrus) ........... 4 gr. (0.268 g)

In a palatable vehicle.

Flavorings and color added.

STORAGE:

Store at controlled room temperature between 15º and 30ºC (59º - 86F).

SHAKE WELL BEFORE USING.

PROTECT FROM FREEZING.

TAKE TIME OBSERVE LABEL DIRECTIONS

MADE IN USA

ISS: 11-11

LOT NO.: EXP. DATE:

Bottle Label

Bottle Label